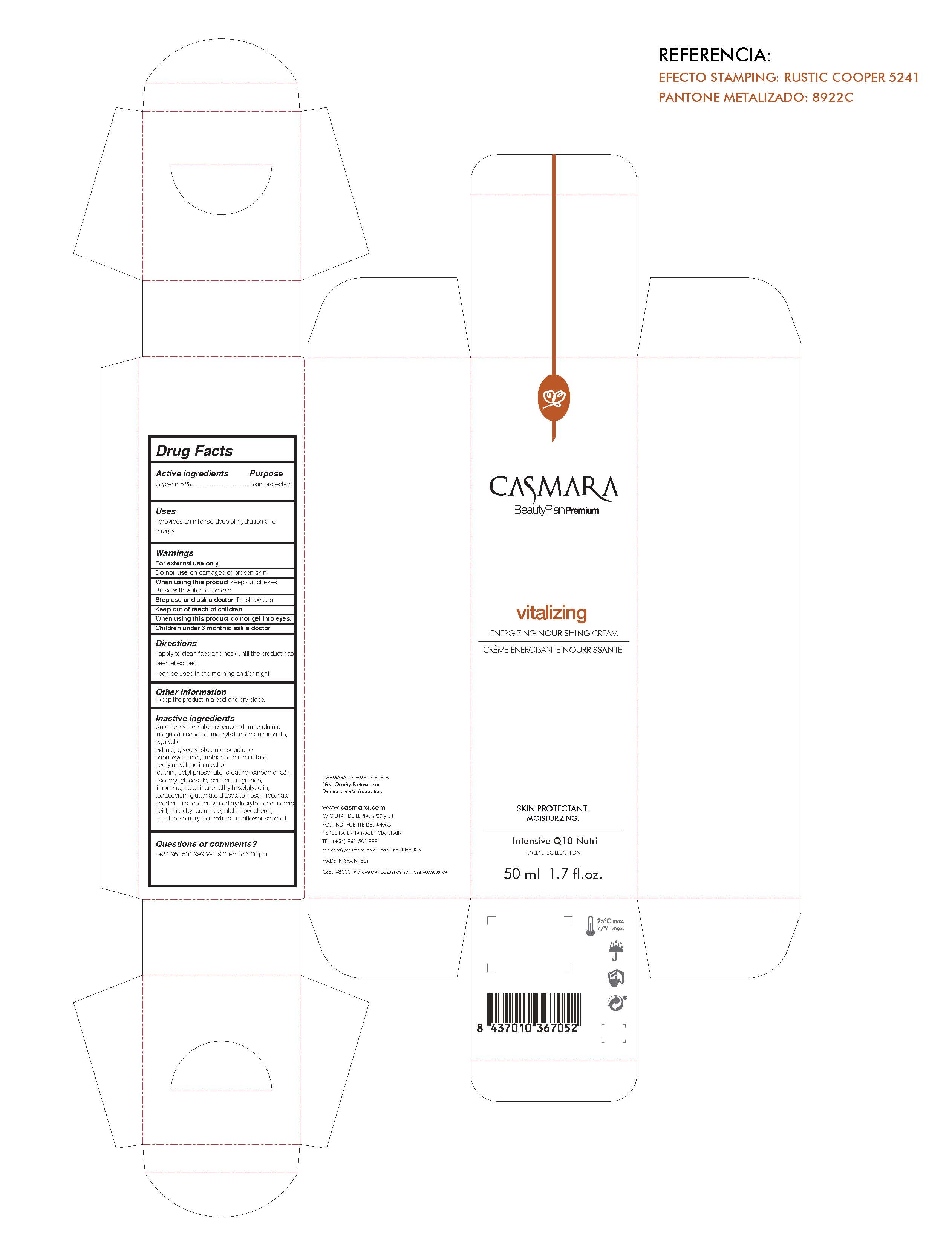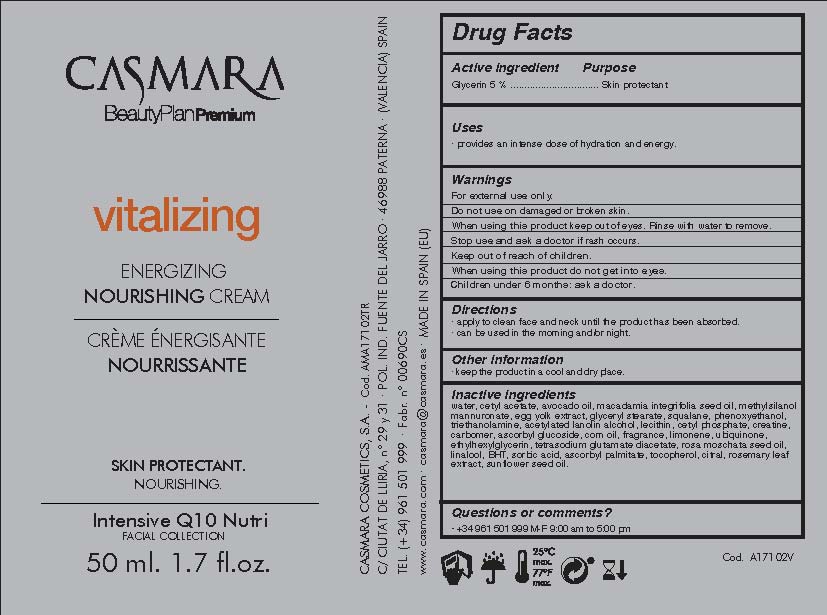 DRUG LABEL: Vitalizing Energizing Nourishing Cream
NDC: 20151-088 | Form: CREAM
Manufacturer: Casmara Cosmetics, SA
Category: otc | Type: HUMAN OTC DRUG LABEL
Date: 20170223

ACTIVE INGREDIENTS: GLYCERIN 5 mg/1 mL
INACTIVE INGREDIENTS: CETYL ACETATE 5.22 mg/1 mL; GLYCERYL STEARATE SE 2.4 mg/1 mL; SUNFLOWER OIL 0.00125 mg/1 mL; CARBOXYPOLYMETHYLENE 0.5 mg/1 mL; ASCORBYL GLUCOSIDE 0.5 mg/1 mL; CORN OIL 0.437 mg/1 mL; ETHYLHEXYLGLYCERIN 0.1 mg/1 mL; WATER 62.046 mg/1 mL; PERFLUNAFENE 0.4 mg/1 mL; PHENOXYETHANOL 0.9 mg/1 mL; LIMONENE, (+)- 0.139 mg/1 mL; TETRASODIUM GLUTAMATE DIACETATE 0.094 mg/1 mL; UBIQUINOL 0.1 mg/1 mL; ROSA MOSCHATA OIL 0.0625 mg/1 mL; LINALOOL, (+)- 0.026 mg/1 mL; BUTYLATED HYDROXYTOLUENE 0.012 mg/1 mL; SORBIC ACID 0.04 mg/1 mL; ASCORBYL PALMITATE 0.0025 mg/1 mL; CITRAL 0.00196 mg/1 mL; .ALPHA.-TOCOPHEROL 0.0025 mg/1 mL; ROSMARINUS OFFICINALIS FLOWER 0.00125 mg/1 mL; HYDROGENATED SOYBEAN LECITHIN 0.75 mg/1 mL; MACADAMIA OIL 4.997 mg/1 mL; CREATINE 0.5 meq/1 mL; AVOCADO OIL 5 mg/1 mL; SODIUM MANNURONATE METHYLSILANOL 3.96 mg/1 mL; EGG YOLK 2.4 meq/1 mL; SQUALANE 2 mg/1 mL; TROLAMINE 0.9 mg/1 mL; ACETYLATED LANOLIN 0.78 meq/1 mL; CETYL PHOSPHATE 0.75 meq/1 mL

Vitalizing Energizing Nourishing Cream

Warnings

For external use only.

Do not use on damaged or broken skin.

When using this product keep our of the eyes. Rinse with water to remove.

Stop use and ask a doctor if rash occurs.

Keep out of reach of children.

Whhen using this product do not get into eyes.

Children under 6 months: as a doctor.

WARNINGS

Stop use and ask a doctor if rash occurs

Children under 6 months: ask a doctor

Warnings

Keep out of reach of children

Questions or comments?

+ 34 961 501 999 M-F 9:00 am to 5:00 pm

Other Information

. keep the product in a cool and dry place

Directions

. apply every day gently onto clean face and neck until the product has been absorbed

. can be used in the morning and/or night

DOSAGE AND ADMINISTRATION

. apply every day gently onto clean dace and neck until the product has been absorbed

. can be used in the morning and/or night

Uses

. provides an intensive dose of hydration and energy

Inactive Ingredients

water, cetyl acetate, persea gratissima (avocado oil), macadamia integrifolia seed oil, methylsilanol mannuronate, egg yolk extract, glyceryl stearate, squalane, phenoxyethanol, triethanolamine, acetylated lanolin alcohol, lecithin, cetyl phosphate, creatine, carbomer, ascorbyl glucoside, corn oil, perfume, limonene, ubiquinone, ethylhexylglycerin, tetrasodium glutamate diacetate, rosa moschata seed oil, linalool, BHT, sorbic acid, ascorbyl palmitate, tocopherol, citral, rosmarinus officinalis (rosmery) leaf extract, helianhus annuus (sunflower) seed oil

Uses

. provides an intense dose of hydration and energy

ACTIVE INGREDIENTS PURPOSE

Glycerin 5%.................... Skin Protectant

See below image

Vitalizing Energizing Nourishing Cream

Skin Protectant

Nourishing

Intensive Q 10 Nuri